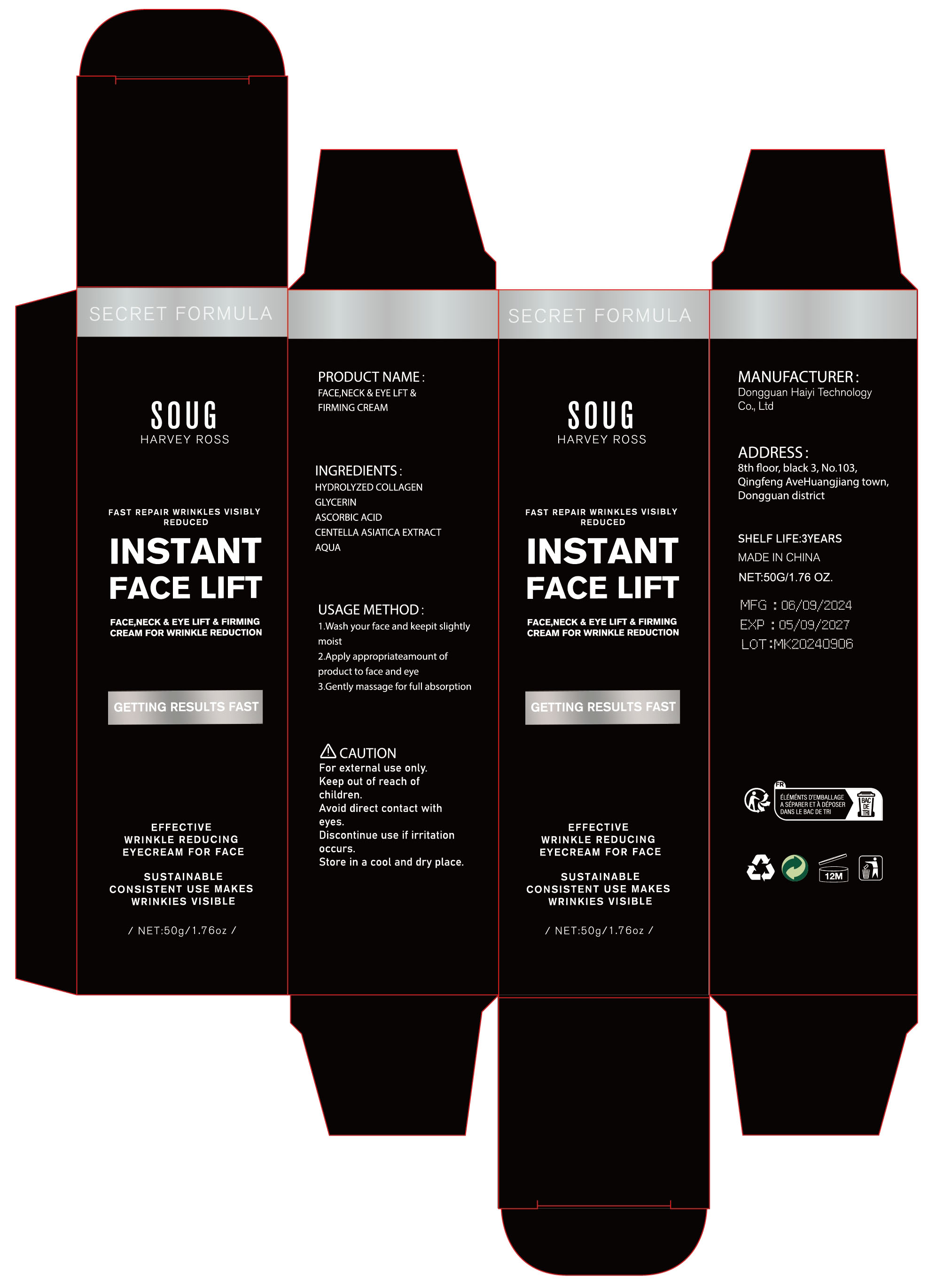 DRUG LABEL: FACE NECK  EYE LFT FIRMING  Cream
NDC: 84732-070 | Form: CREAM
Manufacturer: Dongguan Haiyi Technology Co.,Ltd.
Category: otc | Type: HUMAN OTC DRUG LABEL
Date: 20241028

ACTIVE INGREDIENTS: METHYL CARBOXYMETHYLPHENYL AMINOCARBOXYPROPYLPHOSPHONATE 1 mg/50 g
INACTIVE INGREDIENTS: WATER; ASCORBIC ACID; CENTELLA ASIATICA TRITERPENOIDS; GLYCERIN

Active ingredient

HYDROLYZED COLLAGEN

Inactive ingredient

GLYCERIN,ASCORBIC ACID,CENTELLA ASIATICA EXTRACT,AQUA

Purpose section

EFFECTIVE

WRINKLE REDUCINGEYECREAM FOR FACE
SUSTAINABLE

CONSISTENT USEMAKESWRINKIES VISIBLE

Warning

For external use only.

Keep out of reach ofchildren.

Avoid direct contact witheyes.

Discontinue use if irritationoccurs.

Store in a cool and dry place.

stop use

This product may cause allergic reactions in asmall number of people.
lf you experience any discomfort,please stop using it immediately.

not use

Not suitable for use by children, pregnantor breast feeding people.

OUT OF CHILDREN

KEEP THE PRODUCT OUT OF REACH OF CHILDREN to

HOW TO USE

1.Wash your face and keepit slightly moist

2.Apply appropriateamount ofproduct to face and eye

3.Gently massage for full absorption

Dosage

take an appropriateamount,Use 2-3 times a week